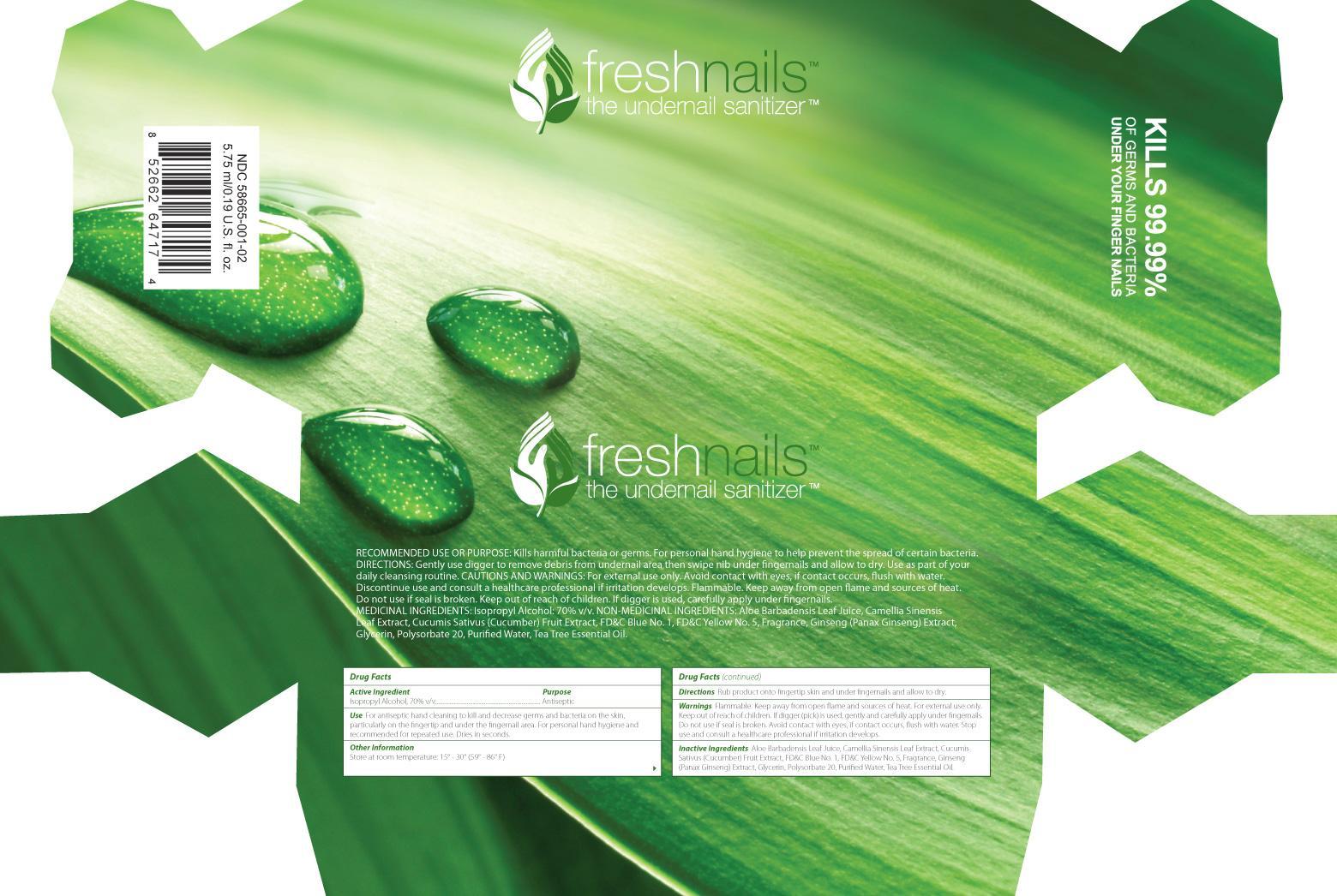 DRUG LABEL: freshnails
NDC: 58665-001 | Form: LIQUID
Manufacturer: TWB Strategic Investments Inc.
Category: otc | Type: HUMAN OTC DRUG LABEL
Date: 20131118

ACTIVE INGREDIENTS: ISOPROPYL ALCOHOL .7 mL/1 mL
INACTIVE INGREDIENTS: ALOE VERA LEAF; GREEN TEA LEAF; CUCUMBER; FD&C BLUE NO. 1; FD&C Yellow No. 5; ASIAN GINSENG; GLYCERIN; Polysorbate 20; WATER; TEA TREE OIL

freshnails

Active Ingredients

Isopropyl Alcohol 70% v/v

Purpose

Antiseptic

Use

- For antiseptic hand cleaning to kill and decrease germs and bacteria on the skin, particularly on the fingertip and under the fingernail area.
- For personal hand hygiene and recommended for repeated use.
- Dries in seconds.

Warnings

- Flammable. Keep away from open flame and sources of heat.
- For external use only.
- Keep out of reach of children.
- If digger (pick) is used, gently and carefully apply under fingernails.
- Do not use if seal is broken.
- Avoid contact with eyes, if contact occurs, flush with water.
- Stop use and consult a healthcare professional if irritation develops.

Keep out of the reach of children

If swallowed, get medical help or contact a Poison Control Center right away.

Directions

- Rub product onto fingertip skin and under fingernails and allow to dry.
- Use as part of your daily cleansing routine.

Other Information

Store at room temperature: 15° - 30° (59° - 86° F)

Inactive Ingredients

Aloe Barbadensis Leaf Juice, Camellia Sinensis Leaf Extract, Cucumis Sativus (Cucumber) Fruit Extract, FD&C Blue No. 1, FD&C Yellow No. 5, Fragrance, Ginseng (Panax Ginseng) Extract, Glycerin, Polysorbate 20, Purified Water, Tea Tree Essential Oil